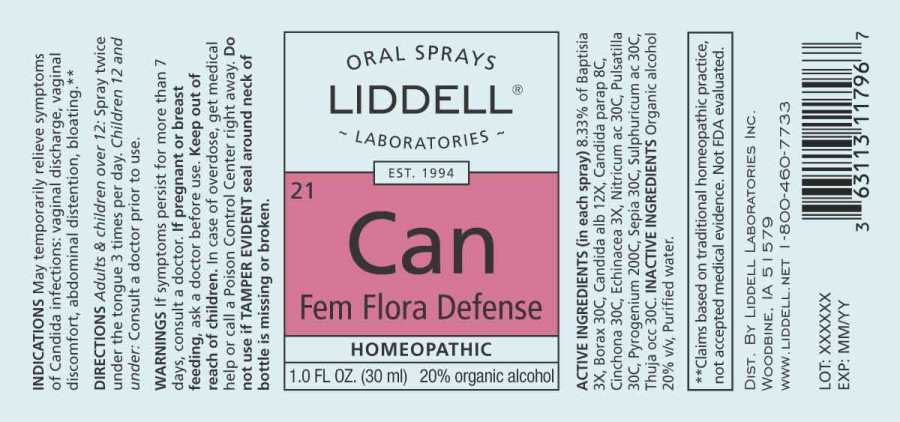 DRUG LABEL: Fem Flora Defense
NDC: 50845-0274 | Form: SPRAY
Manufacturer: Liddell Laboratories, Inc.
Category: homeopathic | Type: HUMAN OTC DRUG LABEL
Date: 20230817

ACTIVE INGREDIENTS: BAPTISIA TINCTORIA ROOT 3 [hp_X]/1 mL; SODIUM BORATE 30 [hp_C]/1 mL; CANDIDA ALBICANS 12 [hp_X]/1 mL; CANDIDA PARAPSILOSIS 8 [hp_C]/1 mL; CINCHONA OFFICINALIS BARK 30 [hp_C]/1 mL; ECHINACEA ANGUSTIFOLIA WHOLE 3 [hp_X]/1 mL; NITRIC ACID 30 [hp_C]/1 mL; PULSATILLA PRATENSIS WHOLE 30 [hp_C]/1 mL; RANCID BEEF 200 [hp_C]/1 mL; SEPIA OFFICINALIS JUICE 30 [hp_C]/1 mL; SULFURIC ACID 30 [hp_C]/1 mL; THUJA OCCIDENTALIS LEAFY TWIG 30 [hp_C]/1 mL
INACTIVE INGREDIENTS: WATER; ALCOHOL

DRUG FACTS:

ACTIVE INGREDIENTS:

(in each spray) 8.33% of Baptisia Tinctoria 3X, Borax 30C, Candida Albicans 12X, Candida Parapsilosis 8C, Cinchona Officinalis 30C, Echinacea (Angustifolia) 3X, Nitricum Acidum 30C, Pulsatilla (Pratensis) 30C, Pyrogenium 200C, Sepia 30C, Sulphuricum Acidum 30C, Thuja Occidentalis 30C.

INDICATIONS:

May temporarily relieve symptoms of Candida infections: vaginal discharge, vaginal discomfort, abdominal distention, bloating.**

**Claims based on traditional homeopathic practice, not accepted medical evidence. Not FDA evaluated.

WARNINGS:

If symptoms persist for more than 7 days, consult a doctor.

If pregnant or breast feeding, ask a doctor before use.

Keep out of reach of children. In case of overdose, get medical help or call a Poison Control Center right away.

Do not use if TAMPER EVIDENT seal around neck of bottle is missing or broken.

Keep out of reach of children. In case of overdose, get medical help or call a Poison Control Center right away.

DIRECTIONS:

Adults and children over 12: Spray twice under the tongue 3 times per day.

Children 12 and under: Consult a doctor prior to use.

INDICATIONS:

May temporarily relieve symptoms of Candida infections: vaginal discharge, vaginal discomfort, abdominal distention, bloating.**

**Claims based on traditional homeopathic practice, not accepted medical evidence. Not FDA evaluated.

INACTIVE INGREDIENTS:

Organic alcohol 20% v/v, Purified water.

QUESTIONS:

DIST. BY LIDDELL LABORATORIES, INC.

WOODBINE, IA 51579

WWW.LIDDELL.NET 1-800-460-7733

PACKAGE LABEL DISPLAY:

ORAL SPRAYS

LIDDELL

LABORATORIES

21Can

Fem Flora Defense

HOMEOPATHIC

1.0 FL OZ. (30 ml)